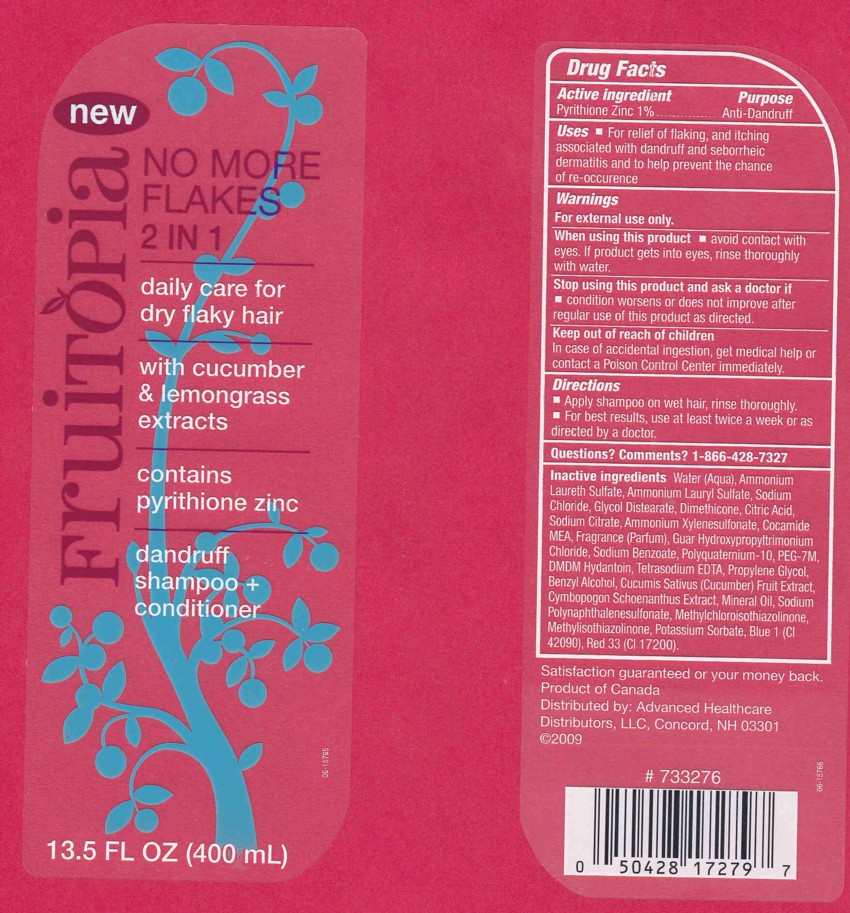 DRUG LABEL: FRUITOPIA
NDC: 59779-421 | Form: LIQUID
Manufacturer: CVS PHARMACY
Category: otc | Type: HUMAN OTC DRUG LABEL
Date: 20120217

ACTIVE INGREDIENTS: PYRITHIONE ZINC 1.0 mL/100 mL
INACTIVE INGREDIENTS: WATER; AMMONIUM LAURETH-2 SULFATE; AMMONIUM LAURYL SULFATE; SODIUM CHLORIDE; GLYCOL DISTEARATE; DIMETHICONE; CITRIC ACID MONOHYDRATE; SODIUM CITRATE; AMMONIUM XYLENESULFONATE; COCO MONOETHANOLAMIDE; GUAR HYDROXYPROPYLTRIMONIUM CHLORIDE (1.7 SUBSTITUENTS PER SACCHARIDE); SODIUM BENZOATE; POLYQUATERNIUM-10 (400 CPS AT 2%); POLYETHYLENE GLYCOL 7000; DMDM HYDANTOIN; EDETATE SODIUM; PROPYLENE GLYCOL; BENZYL ALCOHOL; CUCUMBER; CYMBOPOGON SCHOENANTHUS LEAF; MINERAL OIL; SODIUM 2-NAPHTHALENESULFONATE; METHYLCHLOROISOTHIAZOLINONE; METHYLISOTHIAZOLINONE; POTASSIUM SORBATE; FD&C BLUE NO. 1; D&C RED NO. 33

Drug Facts

ACTIVE INGREDIENT

PYRITHIONE ZINC 1%

PURPOSE

ANTI-DANDRUFF

USES

FOR RELIEF OF FLAKING, AND ITCHING ASSOCIATED WITH DANDRUFF AND SEBORRHEIC DERMATITIS AND TO HELP PREVENT THE CHANCE OF RE-OCCURENCE.

WARNINGS

FOR EXTERNAL USE ONLY.

WHEN USING THIS PRODUCT

AVOID CONTACT WITH EYES. IF PRODUCT GETS INTO EYES, RINSE THOROUGHLY WITH WATER.

STOP USING THIS PRODUCT AND ASK A DOCTOR IF

CONDITION WORSENS OR DOES NOT IMPROVE AFTER REGULAR USE OF THIS PRODUCT AS DIRECTED.

KEEP OUT OF REACH OF CHILDREN

IN CASE OF ACCIDENTAL INGESTION, GET MEDICAL HELP OR CONTACT A POISON CONTROL CENTER IMMEDIATELY.

DIRECTIONS

APPLY SHAMPOO ON WET HAIR, RINSE THOROUGHLY. FOR BEST RESULTS, USE AT LEAST TWICE A WEEK OR AS DIRECTED BY A DOCTOR.

QUESTIONS? COMMENTS?

1-866-428-7327

INACTIVE INGREDIENTS

WATER (AQUA), AMMONIUM LAURETH SULFATE, AMMONIUM LAURYL SULFATE, SODIUM CHLORIDE, GLYCOL DISTEARATE, DIMETHICONE, CITRIC ACID, SODIUM CITRATE, AMMONIUM XYLENESULFONATE, COCAMIDE MEA, FRAGRANCE (PARFUM), GUAR HYDROXYPROPYLTRIMONIUM CHLORIDE, SODIUM BENZOATE, POLYQUATERNIUM-10, PEG-7M, DMDM HYDANTOIN, TETRASODIUM EDTA, PROPYLENE GLYCOL, BENZYL ALCOHOL, CUCUMIS SATIVUS (CUCUMBER) FRUIT EXTRACT, CYMBOPOGON SCHOENANTHUS EXTRACT, MINERAL OIL, SODIUM POLYNAPHTHALENESULFONATE, METHYLCHLOROISOTHIAZOLINONE, METHYLISOTHIAZOLINONE, POTASSIUM SORBATE, BLUE 1 (CI 42090), RED 33 (CI 17200).